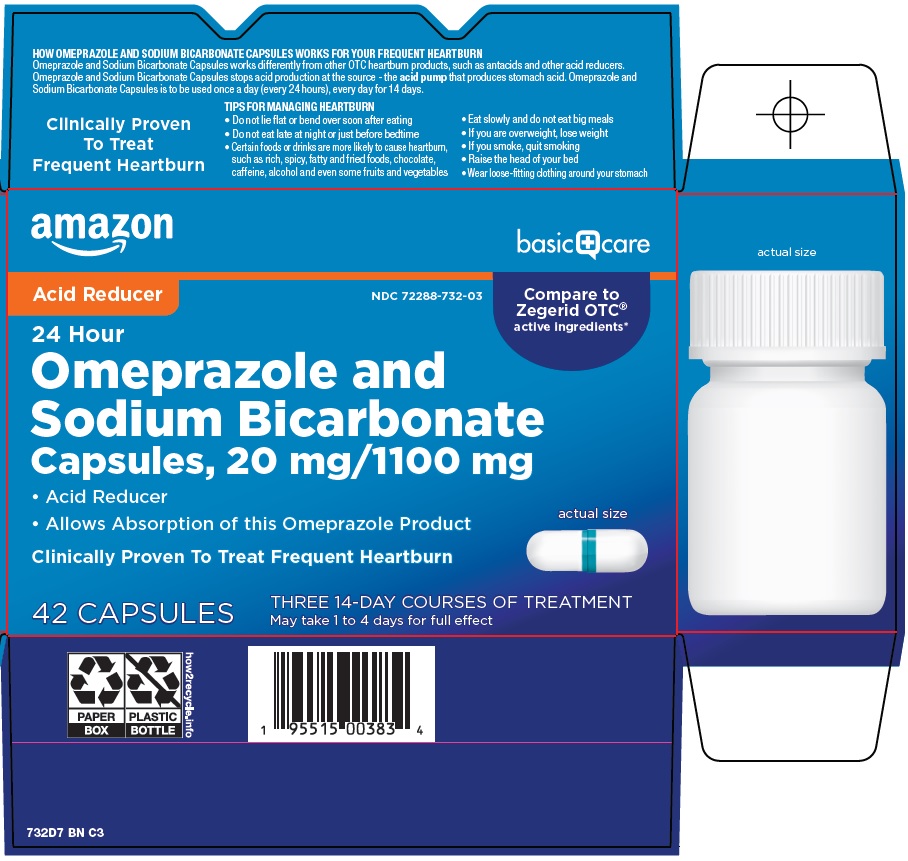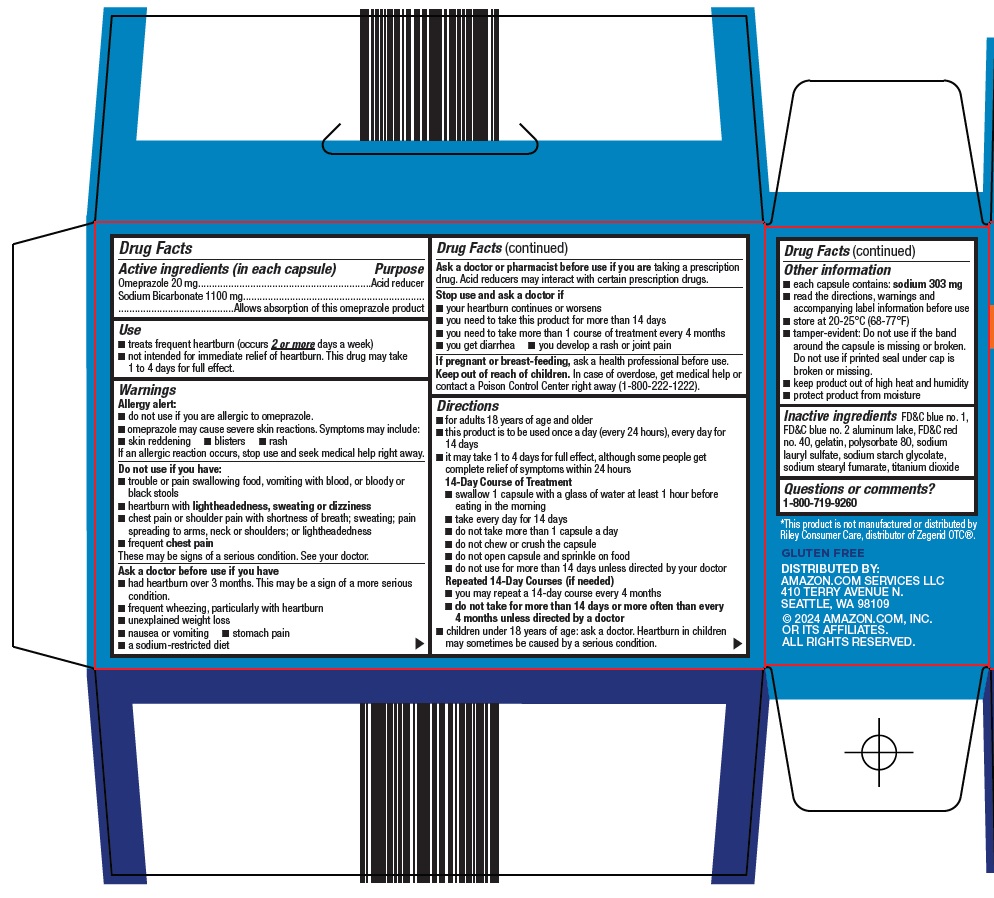 DRUG LABEL: basic care omeprazole and sodium bicarbonate
NDC: 72288-732 | Form: CAPSULE, GELATIN COATED
Manufacturer: Amazon.com Services LLC
Category: otc | Type: HUMAN OTC DRUG LABEL
Date: 20251104

ACTIVE INGREDIENTS: OMEPRAZOLE 20 mg/1 1; SODIUM BICARBONATE 1100 mg/1 1
INACTIVE INGREDIENTS: FD&C BLUE NO. 1; FD&C BLUE NO. 2 ALUMINUM LAKE; FD&C RED NO. 40; GELATIN, UNSPECIFIED; POLYSORBATE 80; SODIUM LAURYL SULFATE; SODIUM STARCH GLYCOLATE TYPE A; SODIUM STEARYL FUMARATE; TITANIUM DIOXIDE

Amazon Omeprazole and Sodium Bicarbonate Drug Facts

Active ingredients (in each capsule)

Omeprazole 20 mg

Sodium Bicarbonate 1100 mg

Purpose

Acid reducer

Allows absorption of this omeprazole product

Use

- treats frequent heartburn (occurs 2 or more days a week)
- not intended for immediate relief of heartburn. This drug may take 1 to 4 days for full effect.

Warnings

Allergy alert:

- do not use if you are allergic to omeprazole.
- omeprazole may cause severe skin reactions. Symptoms may include:
  - skin reddening
  - blisters
  - rash
    If an allergic reaction occurs, stop use and seek medical help right away.

Do not use if you have:

- trouble or pain swallowing food, vomiting with blood, or bloody or black stools
- heartburn with lightheadedness, sweating or dizziness
- chest pain or shoulder pain with shortness of breath; sweating; pain spreading to arms, neck or shoulders; or lightheadedness
- frequent chest pain

These may be signs of a serious condition. See your doctor.

Ask a doctor before use if you have

- had heartburn over 3 months. This may be a sign of a more serious condition.
- frequent wheezing, particularly with heartburn
- unexplained weight loss
- nausea or vomiting
- stomach pain
- a sodium-restricted diet

Ask a doctor or pharmacist before use if you are

taking a prescription drug. Acid reducers may interact with certain prescription drugs.

Stop use and ask a doctor if

- your heartburn continues or worsens
- you need to take this product for more than 14 days
- you need to take more than 1 course of treatment every 4 months
- you get diarrhea
- you develop a rash or joint pain

If pregnant or breast-feeding,

ask a health professional before use.

Keep out of reach of children.

In case of overdose, get medical help or contact a Poison Control Center right away (1-800-222-1222).

Directions

- for adults 18 years of age and older
- this product is to be used once a day (every 24 hours), every day for 14 days
- it may take 1 to 4 days for full effect, although some people get complete relief of symptoms within 24 hours
14-Day Course of Treatment
  1. swallow 1 capsule with a glass of water at least 1 hour before eating in the morning
  2. take every day for 14 days
  3. do not take more than 1 capsule a day
  4. do not chew or crush the capsule
  5. do not open capsule and sprinkle on food
  6. do not use for more than 14 days unless directed by your doctor
Repeated 14-Day Courses (if needed)
  1. you may repeat a 14-day course every 4 months
  2. do not take for more than 14 days or more often than every 4 months unless directed by a doctor
- children under 18 years of age: ask a doctor. Heartburn in children may sometimes be caused by a serious condition.

Other information

- each capsule contains: sodium 303 mg
- read the directions, warnings and accompanying label information before use
- store at 20-25°C (68-77°F)
- tamper-evident: Do not use if the band around the capsule is missing or broken. Do not use if printed seal under cap is broken or missing.
- keep product out of high heat and humidity
- protect product from moisture

Inactive ingredients

FD&C blue no. 1, FD&C blue no. 2 aluminum lake, FD&C red no. 40, gelatin, polysorbate 80, sodium lauryl sulfate, sodium starch glycolate, sodium stearyl fumarate, titanium dioxide

Questions or comments?

1-800-719-9260

Package/Label Principal Display Panel

amazon

basic care

Acid Reducer

Compare to Zegerid OTC® active ingredients

24 Hour

Omeprazole and Sodium Bicarbonate

Capsules, 20 mg/1100 mg

• Acid Reducer

• Allows Absorption of this Omeprazole Product

actual size

Clinically Proven To Treat Frequent Heartburn

42 CAPSULES

THREE 14-DAY COURSES OF TREATMENT

May take 1 to 4 days for full effect